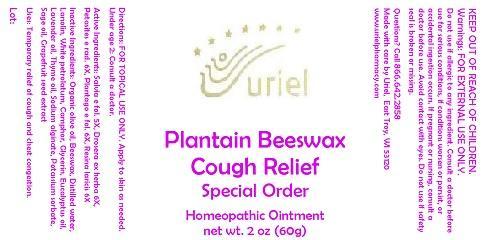 DRUG LABEL: Plantain Beeswax Cough Relief Special Order
NDC: 48951-8276 | Form: OINTMENT
Manufacturer: Uriel Pharmacy Inc.
Category: homeopathic | Type: HUMAN OTC DRUG LABEL
Date: 20141104

ACTIVE INGREDIENTS: SAGE 5 [hp_X]/1 g; DROSERA ROTUNDIFOLIA 6 [hp_X]/1 g; PETASITES HYBRIDUS ROOT 6 [hp_X]/1 g; PLANTAGO MAJOR LEAF 6 [hp_X]/1 g; LARIX DECIDUA RESIN 6 [hp_X]/1 g
INACTIVE INGREDIENTS: OLIVE OIL; YELLOW WAX; WATER; LANOLIN; PETROLATUM; CAMPHOR (NATURAL); GLYCERIN; EUCALYPTUS OIL; LAVENDER OIL; THYME OIL; SODIUM ALGINATE; POTASSIUM SORBATE; SAGE OIL; CITRUS PARADISI SEED

Plantain Beeswax Cough Relief Special Order

INDICATIONS AND USAGE

Directions: FOR TOPICAL USE ONLY.

DOSAGE AND ADMINISTRATION

Apply to skin as needed. Under age 2: Consult a doctor.

ACTIVE INGREDIENT

Active Ingredients: Salvia e fol. 5X, Drosera ex herba 6X, Petasites e rad. 6X, Plantago e fol. 6X, Resina laricis 6X

INACTIVE INGREDIENT

Inactive Ingredients: Organic olive oil, Beeswax, Distilled water, Lanolin, White petrolatum, Camphor, Glycerin, Eucalyptus oil, Lavender oil, Thyme oil, Sodium alginate, Potassium sorbate, Sage oil, Grapefruit seed extract

PURPOSE

Uses: Temporary relief of cough and chest congestion.

KEEP OUT OF REACH OF CHILDREN.

WARNINGS

Warnings: FOR EXTERNAL USE ONLY. Do not use if allergic to any ingredient. Consult a doctor before use for serious conditions, if conditions worsen or persist, or accidental ingestion occurs. If pregnant or nursing, consult a doctor before use. Avoid contact with eyes. Do not use if safety seal is broken or missing.

QUESTIONS

Questions? Call 866.642.2858 Made with care by Uriel, East Troy, WI 53120 www.urielpharmacy.com